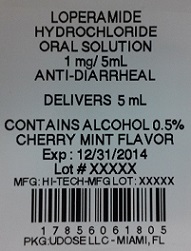 DRUG LABEL: Loperamide Hydrochloride
NDC: 17856-0618 | Form: SOLUTION
Manufacturer: Atlantic Biologicals Corps
Category: otc | Type: HUMAN OTC DRUG LABEL
Date: 20191016

ACTIVE INGREDIENTS: LOPERAMIDE HYDROCHLORIDE 1 mg/5 mL
INACTIVE INGREDIENTS: ALCOHOL; ANHYDROUS CITRIC ACID; BENZOIC ACID; CHERRY; GLYCERIN; MINT; PROPYLENE GLYCOL; SODIUM BENZOATE; SORBITOL; SUCROSE; WATER

Drug Facts

Active ingredient

(in each 5 mL teaspoonful)

Loperamide HCl 1 mg

Purpose

Antidiarrheal

Uses

- controls the symptoms of diarrhea, including Traveler's Diarrhea

Warnings

Do not use if you have ever had a rash or other allergic reaction to loperamide HCl Alergy alert:

if you have bloody or black stool Do not use

Ask a doctor before use if you have

- high fever (greater than 101°F)
- mucus present in your stool
- a history of liver disease

taking antibiotics Ask doctor or pharmacist before use if you are

diarrhea lasts for more than 2 days Stop use and ask a doctor if

, ask a health professional before use If pregnant or breast-feeding

Keep out of reach of children.

In case of overdose, get medical help or contact a Poison Control Center right away.

Directions

- use enclosed dosage cup to accurately measure dosage as noted below
- drink plenty of clear fluids to help prevent dehydration, which may accompany diarrhea
- find right dose on chart. If possible, use weight to dose; otherwise, use age.

adults and children 12 years and older | 4 teaspoonfuls (1 dosage cup) after the first loose bowel movement; 2 teaspoonfuls (1/2 dosage cup) after each subsequent loose bowel movement; but no more than 8 teaspoonfuls a day
children 9-11 years (60-95 lbs) | 2 teaspoonfuls (1/2 dosage cup) after the first loose bowel movement; 1 teaspoonful (1/4 dosage cup) after each subsequent loose bowel movement; but no more than 6 teaspoonfuls a day
children 6-8 years (48-59 lbs) | 2 teaspoonfuls (1/2 dosage cup) after the first loose bowel movement; 1 teaspoonful (1/4 dosage cup) after each subsequent loose bowel movement; but no more than 4 teaspoonfuls a day
children under 6 years (up to 47 lbs) | ask a doctor (not intended for use in children under 6 years old)

Other information

- avoid excess heat
- store at room temperature, 15° - 30°C (59° - 86°F)

Inactive ingredients

alcohol (0.5%), benzoic acid, cherry flavor, glycerin, mint flavor, propylene glycol, purified water, sodium benzoate, sorbitol solution, sucrose. Citric acid may be used to adjust pH

Questions or comments?

Call 1-800-262-9010

Mon. - Thurs. 9:00 am - 4:30 pm EST,

Fri. 9:00 am - 2:30 pm EST

Serious side effects associated with use of this product may be reported to this number.

Manufactured by:

Hi-Tech Pharmacal Co., Inc.

Amityville, NY 11701

Rev. 618:05 4/12